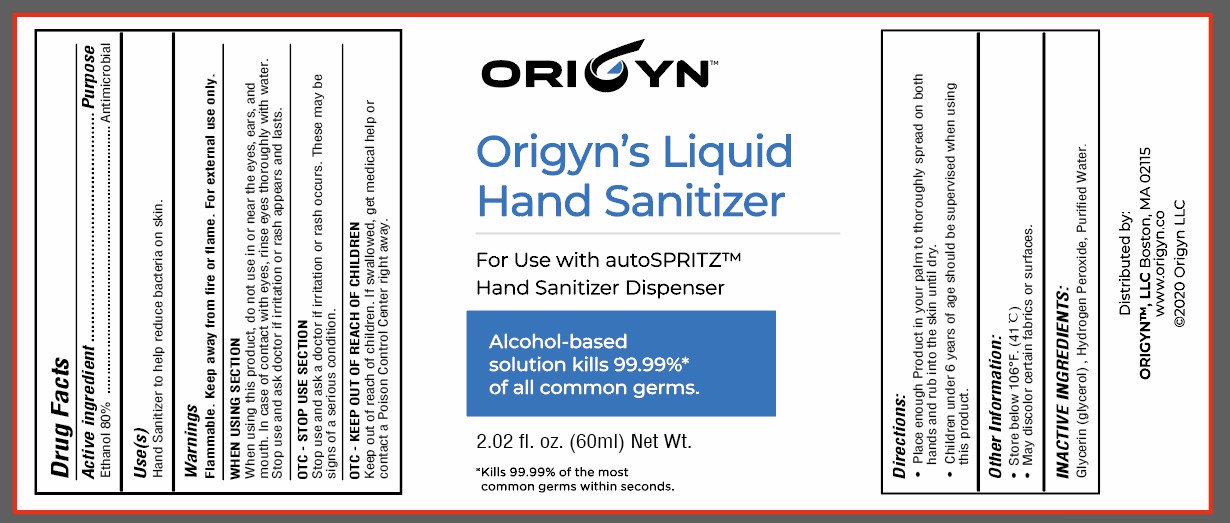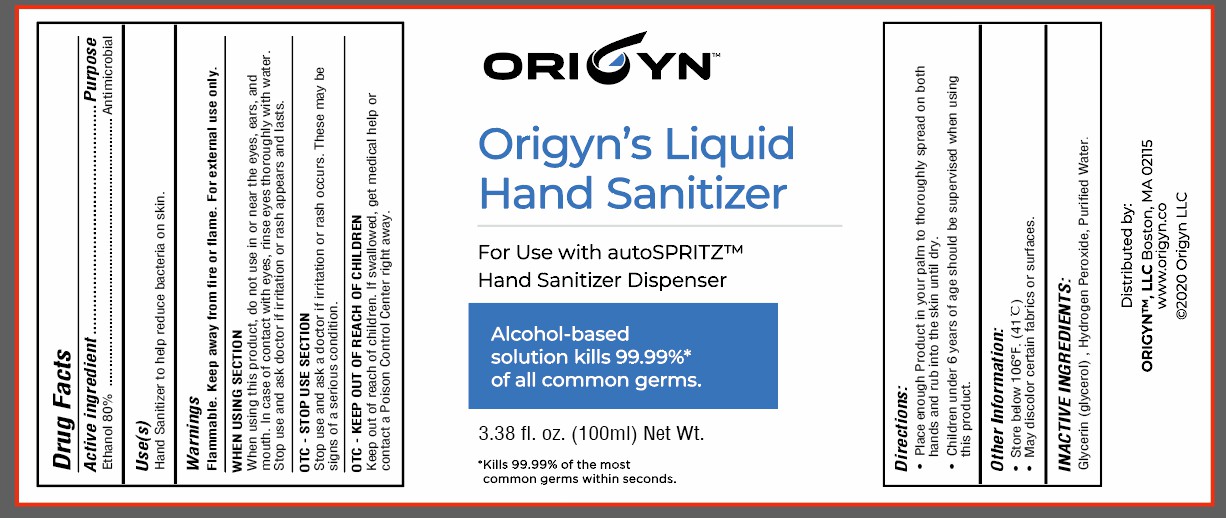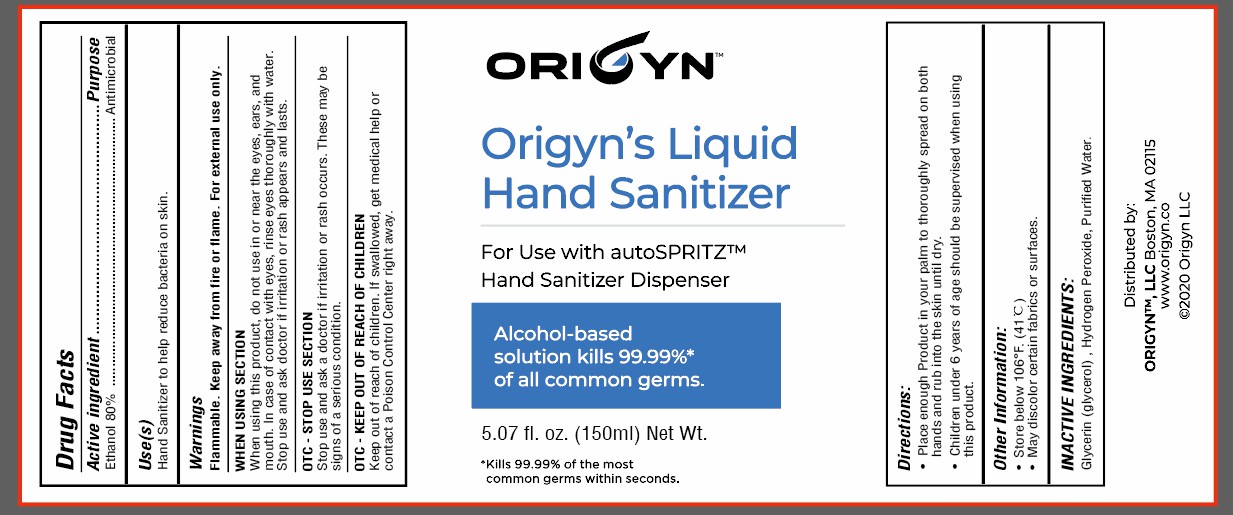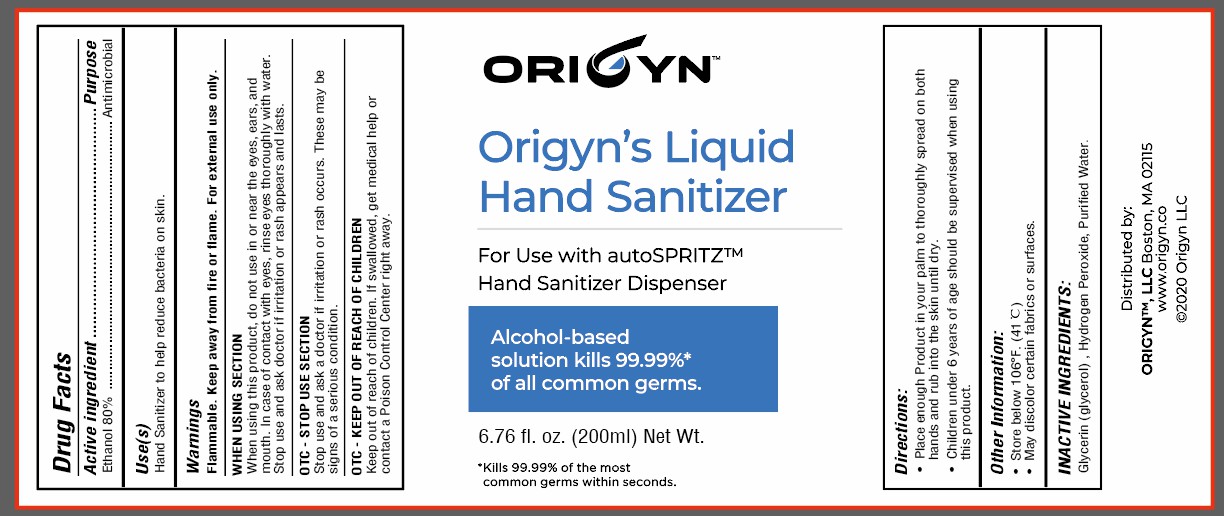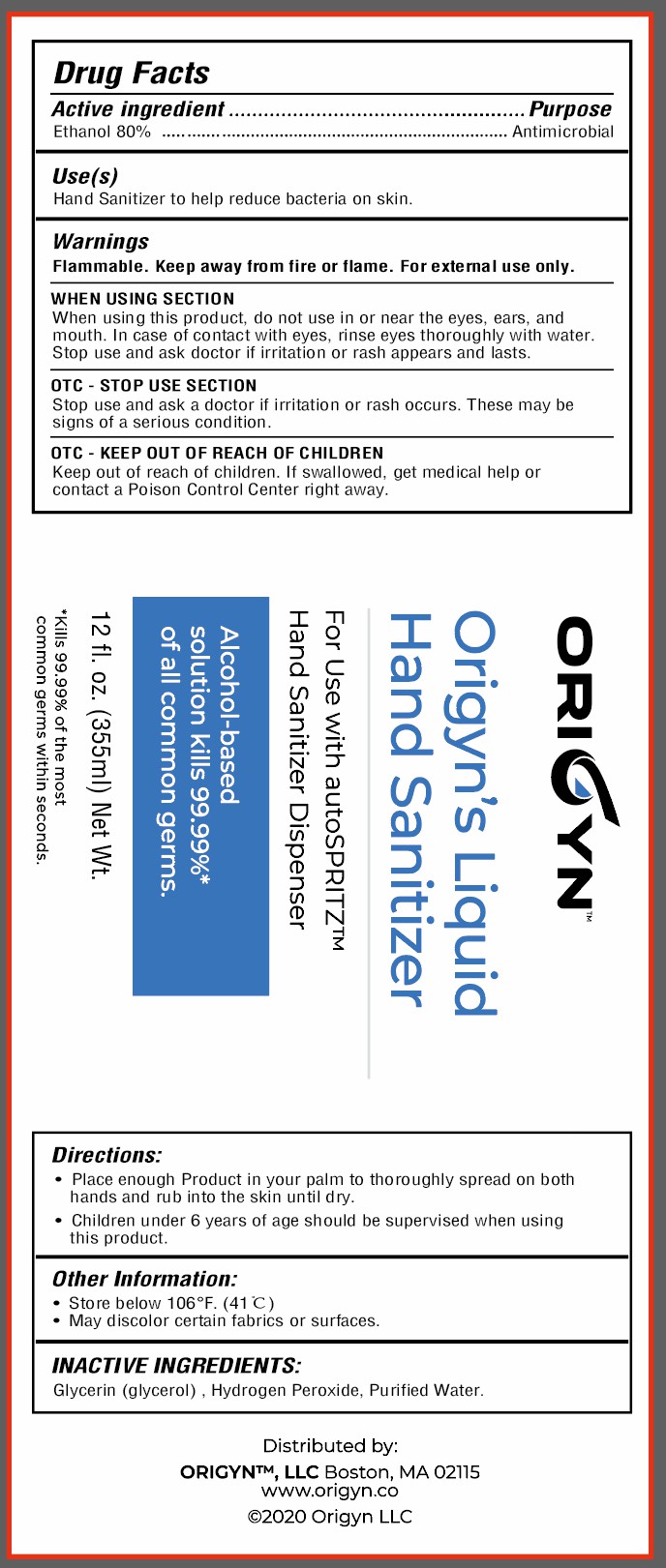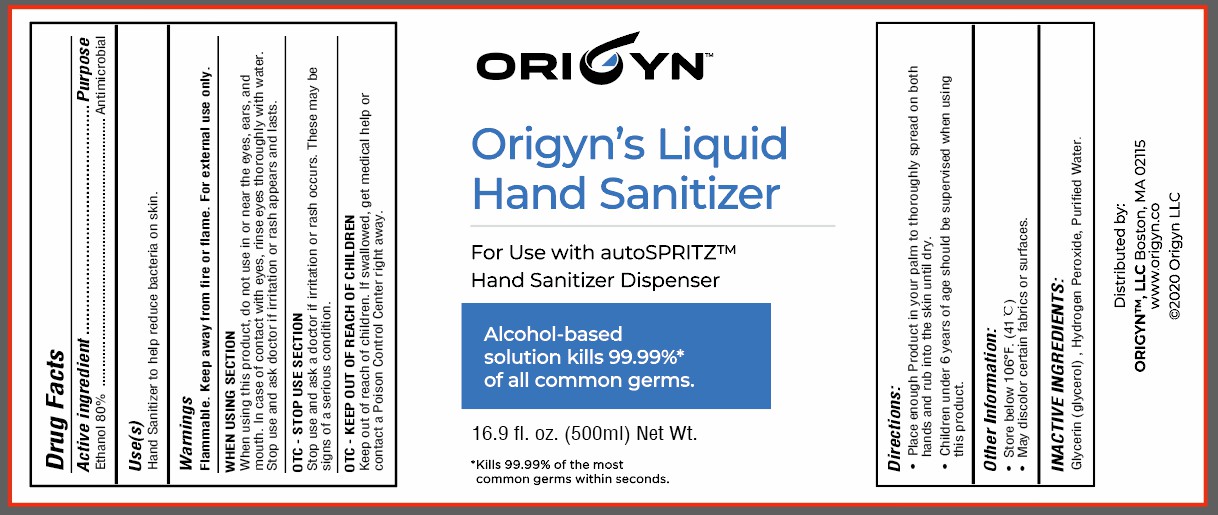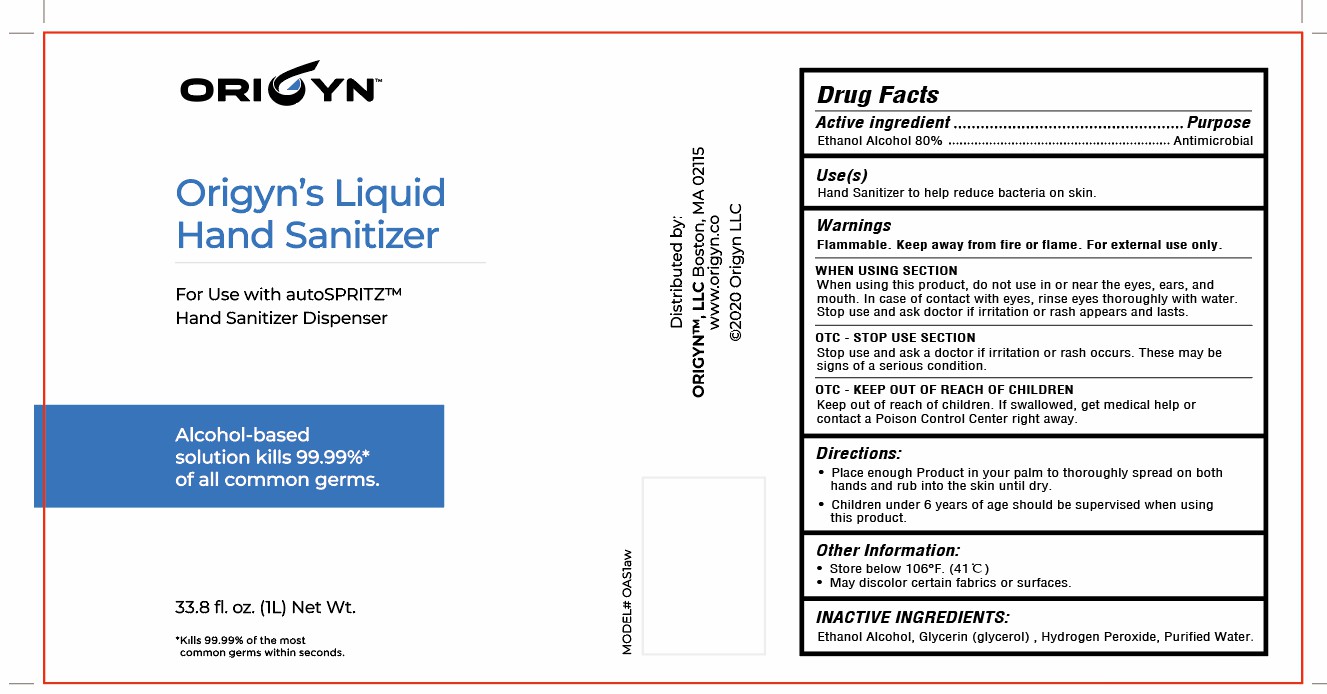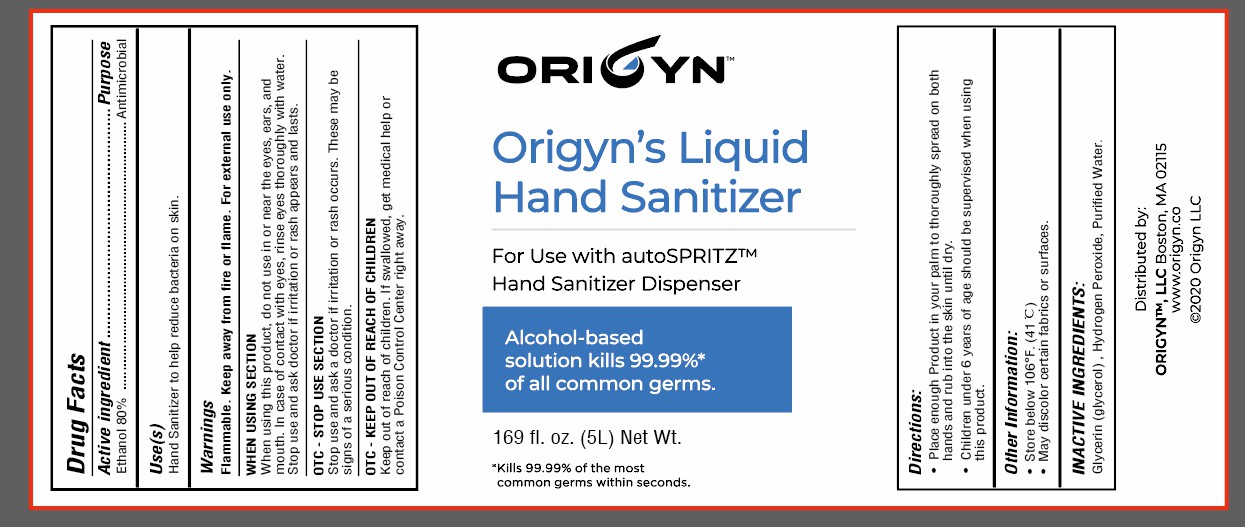 DRUG LABEL: Origyn Liquid Hand Sanitizer
NDC: 75605-007 | Form: LIQUID
Manufacturer: Guangzhou Shiruoni Cosmetics Co.,Ltd
Category: otc | Type: HUMAN OTC DRUG LABEL
Date: 20200817

ACTIVE INGREDIENTS: ALCOHOL 80 mL/100 mL
INACTIVE INGREDIENTS: GLYCERIN; HYDROGEN PEROXIDE; WATER

75605-007
Origyn Liquid Hand Sanitizer

Active Ingredient(s)

Ethanol 80%

Purpose

Antimicrobial

Use

Hand Sanitizer to help reduce bacteria on skin

Directions

Place enough Product in your palm to thoroughly spread on both
hands and rub into the skin until dry.
Children under 6 years of age should be supervised when using
this product.

CAUTION WARNING

Flammable. Keep away from fire or flame. For external use only.

Other information

Store below 106°F. (41℃)
May discolor certain fabrics or surfaces.

Inactive ingredients

Glycerin (glycerol) , Hydrogen Peroxide, Purified Water.

When using this product, do not use in or near the eyes, ears, and
mouth. In case of contact with eyes, rinse eyes thoroughly with water.
Stop use and ask doctor if irritation or rash appears and lasts.

Stop use and ask a doctor if irritation or rash occurs. These may be
signs of a serious condition.

Keep out of reach of children. If swallowed, get medical help or
contact a Poison Control Center right away.